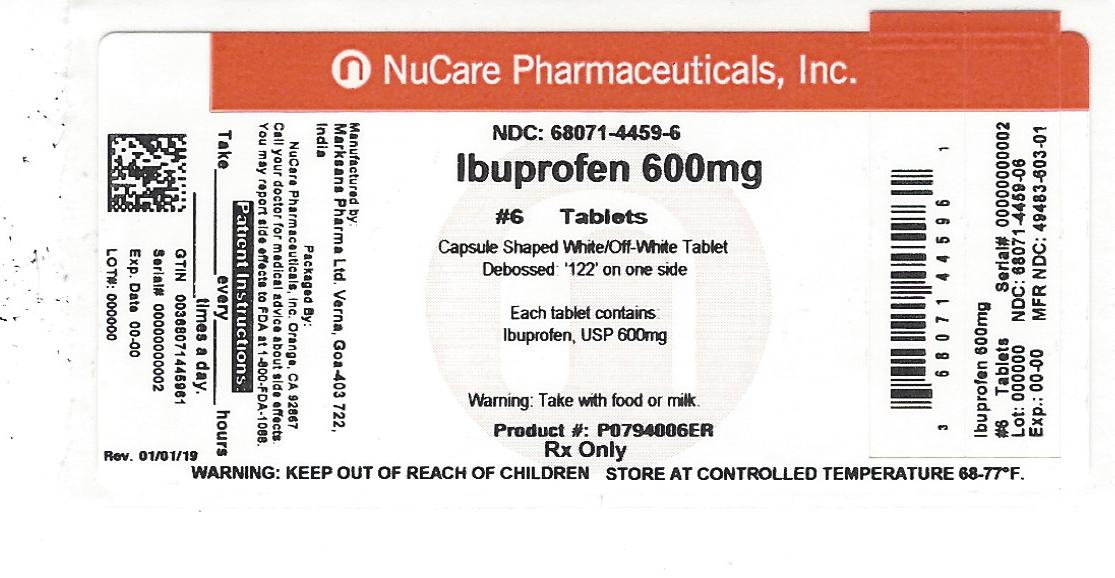 DRUG LABEL: IBUPROFEN
NDC: 68071-4459 | Form: TABLET, FILM COATED
Manufacturer: NuCare Pharmaceuticals,Inc.
Category: prescription | Type: HUMAN PRESCRIPTION DRUG LABEL
Date: 20240610

ACTIVE INGREDIENTS: IBUPROFEN 600 mg/1 1
INACTIVE INGREDIENTS: SILICON DIOXIDE; CROSCARMELLOSE SODIUM; MAGNESIUM STEARATE; CELLULOSE, MICROCRYSTALLINE; POLYETHYLENE GLYCOL, UNSPECIFIED; POLYVINYL ALCOHOL; STARCH, PREGELATINIZED CORN; TALC; TITANIUM DIOXIDE

HOW SUPPLIED

600mg (white to off white, capsule shaped, biconvex, film coated tablets debossed with 122 on one side and plain on the other side.

NDC 68071-4459-6 BOTTLES OF 6